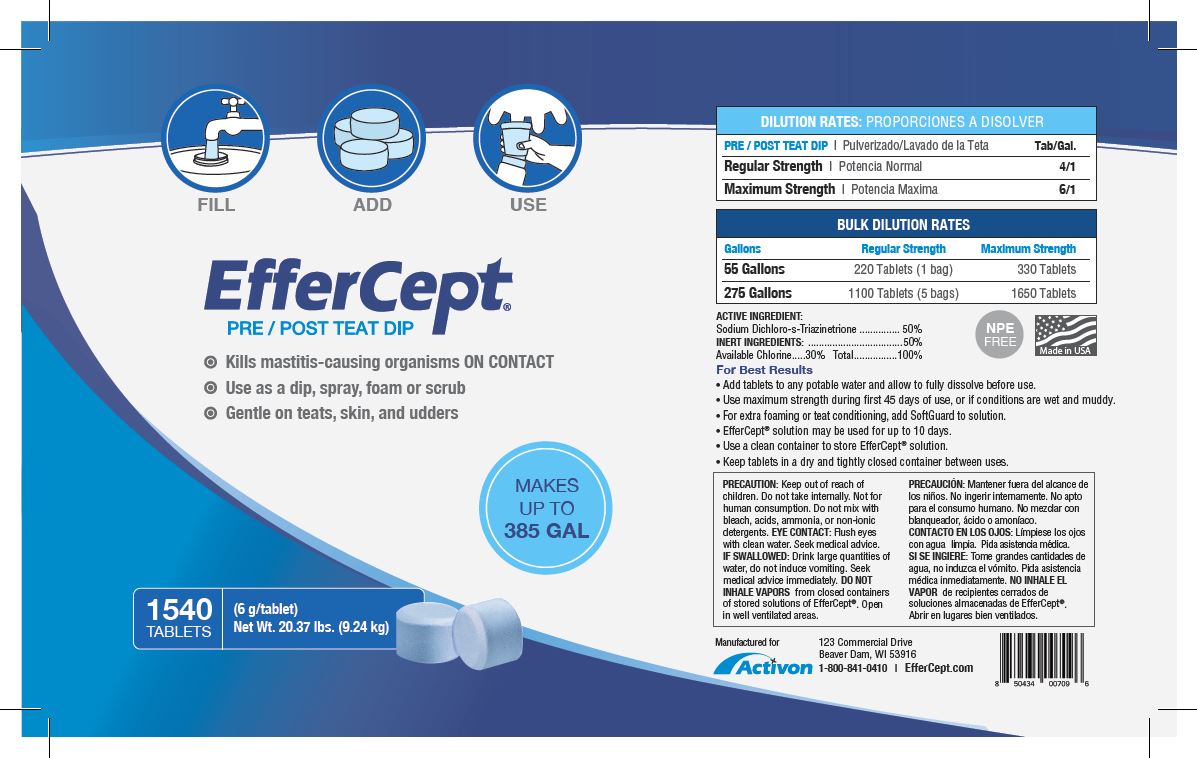 DRUG LABEL: EfferCept
NDC: 14925-301 | Form: FOR SOLUTION
Manufacturer: Activon
Category: animal | Type: OTC ANIMAL DRUG LABEL
Date: 20221219

ACTIVE INGREDIENTS: TROCLOSENE SODIUM 3 g/6 g

Package Labeling

DOSAGE AND ADMINISTRATION

DILUTION RATES

PRE/POST TEAT DIP Tab/Gal.

Regular Strength 2/1

Maximum Strength 3/1

BULK DILUTION RATES

Gallons Regular Strength Maximum Strength

55 Gallons 220 Tablets (1 bag) 330 Tablets

275 Gallons 1100 Tablets (5 bags) 1650 Tablets

ACTIVE INGREDIENT:

Sodium Dichloro-s-Triazinetrione................50%

INERT INGREDIENTS:.........................50%

Available Chlorine....30% Total...............100%

STORAGE AND HANDLING

For Best Results

- Add tablets to any potable water and allow to fully dissolve before use.
- Use maximum strength during first 45 days of use, or if conditions are wet and muddy.
- For extra foaming of teat conditioning, add SoftGuard to solution.
- EfferCept solution may be used for up to 10 days.
- Use a clean container to store EfferCept solution.
- Keep tablets in a dry and tightly closed container between uses.

PRECAUTIONS

PRECAUTION: Keep out of reach of children. Do not take Internally. Not for human consumption. Do not mix with bleach, acids, ammonia, or non-ionic detergents.

EYE CONTACT: Flush eyes with clean water. Seek medical advice.

IF SWALLOWED: Drink large quantities of water, do not induce vomiting. Seek medical advice immediately.

DO NOT INHALE VAPORS from closed containers of stored solutions of EfferCept. Open in well ventilated areas.

PACKAGE LABEL

FILL ADD USE

MAKES UP TO XX GAL

EfferCept

PRE/ POST TEAT DIP

Kills mastitis-causing organisms ON CONTACT

Use as a dip, spray, foam or scrub

Gentle on teats, skin, and udders

1540 TABLETS

(6 g/tablet)

Net WT. 20.37 lbs. (9.24 kg)